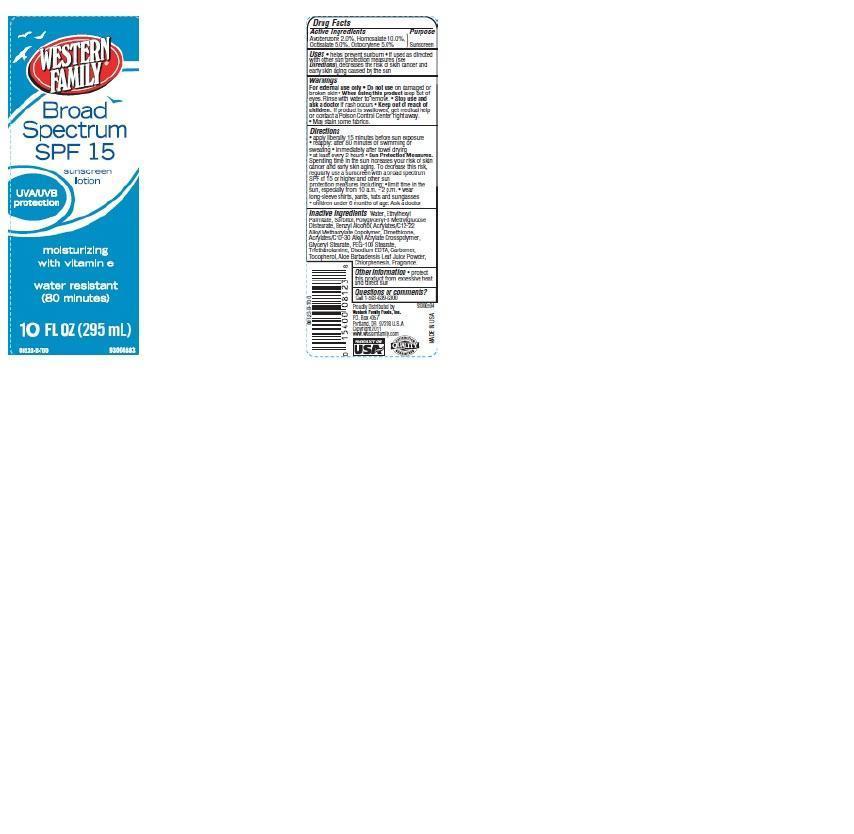 DRUG LABEL: Western FAMILY
NDC: 55312-017 | Form: LOTION
Manufacturer: WESTERN FAMILY FOODS, INC.
Category: otc | Type: HUMAN OTC DRUG LABEL
Date: 20140707

ACTIVE INGREDIENTS: AVOBENZONE 2 g/100 g; HOMOSALATE 10 g/100 g; OCTISALATE 5 g/100 g; OCTOCRYLENE 5 g/100 g
INACTIVE INGREDIENTS: WATER; ETHYLHEXYL PALMITATE; SORBITOL; BENZYL ALCOHOL; DIMETHICONE; GLYCERYL MONOSTEARATE; PEG-100 STEARATE; TROLAMINE; EDETATE DISODIUM; TOCOPHEROL; ALOE VERA LEAF; CHLORPHENESIN

Drug Facts

Active ingredients

Avobenzone 2.0%

Homosalate 10.0%

Octisalate 5.0%

Octocrylene 5.0%

Purpose

Sunscreen

Uses

- Helps prevent sunburn
- If used as directed with other sun protection measures (see Directions), decrease the risk of skin cancer and early skin aging caused by the sun.

Warnings

For external use only. Do not use on damaged or broken skin.

When using this product

Keep out of eyes. Rinse with water to remove.

Stop use and ask a doctor

if rash occurs

Keep out of reach of children

If swallowed, get medical help or contact a Poison Control Center right away. May stain some fabrics.

Directions

- apply liberally 15 minutes before sun exposure
- reapply
- after 80 minutes of swimming or sweating
- immediately after towel drying
- at least every 2 hours
- Sun Protection Measures: Spending time in the sun increases your risk of skin cancer and early skin aging. To decrease this risk, regularly use a sunscreen with a broad spectrum SPF of 15 or higher and other sun protection measures including:
- limit time in the sun, especially from 10 a.m. - 2 p.m.
- wear long-sleeve shirts, pants, hats and sunglasses
- children under 6 months of age: Ask a doctor

Inactive ingredients

Water, Ethylhexyl Palmitate, Sorbitol, Polyglyceryl-3 Methylglucose Distearate, Benzyl Alcohol, Acrylates/C12-22 Alkyl Methacrylate Copolymer, Dimethicone, Acrylates/C10-30 Alkyl Acrylate Crosspolymer, Glyceryl Stearate, PEG-100 Stearate, Triethanolamine, Disodium EDTA, Carbomer, Tocopherol, Aloe Barbadensis Leaf Juice Powder, Chlorphenesin, Fragrance.

Other Information

- protect this product from excessive heat and direct sun

Principal Display Panel

WESTERN FAMILY

Broad Spectrum

SPF 15

sunscreen lotion

UVA/UVB protection

moisturizing with vitamin e

water resistant

(80 minutes)

10 FL OZ (295 mL)

Questions or comments?

Call 1-503-639-6300